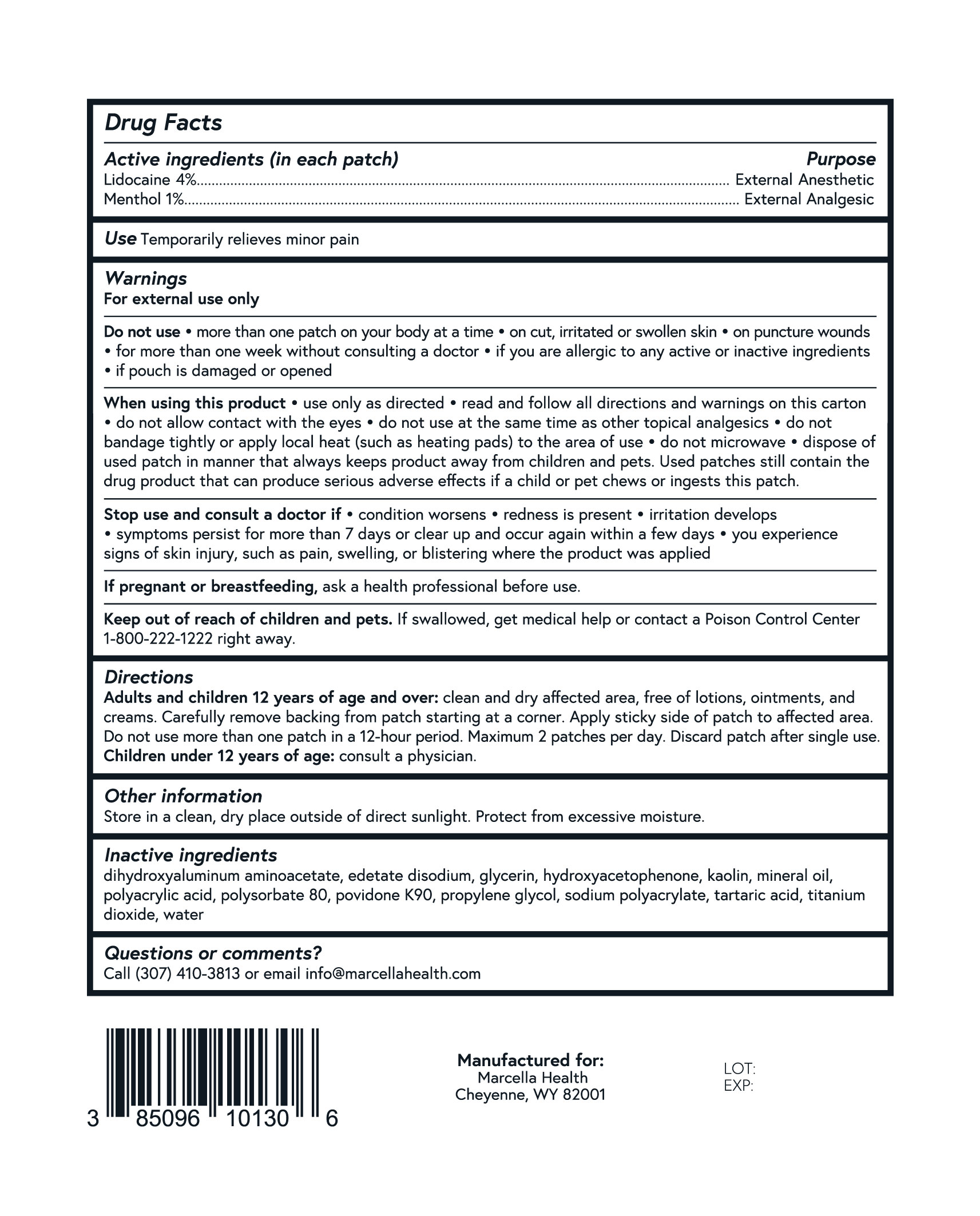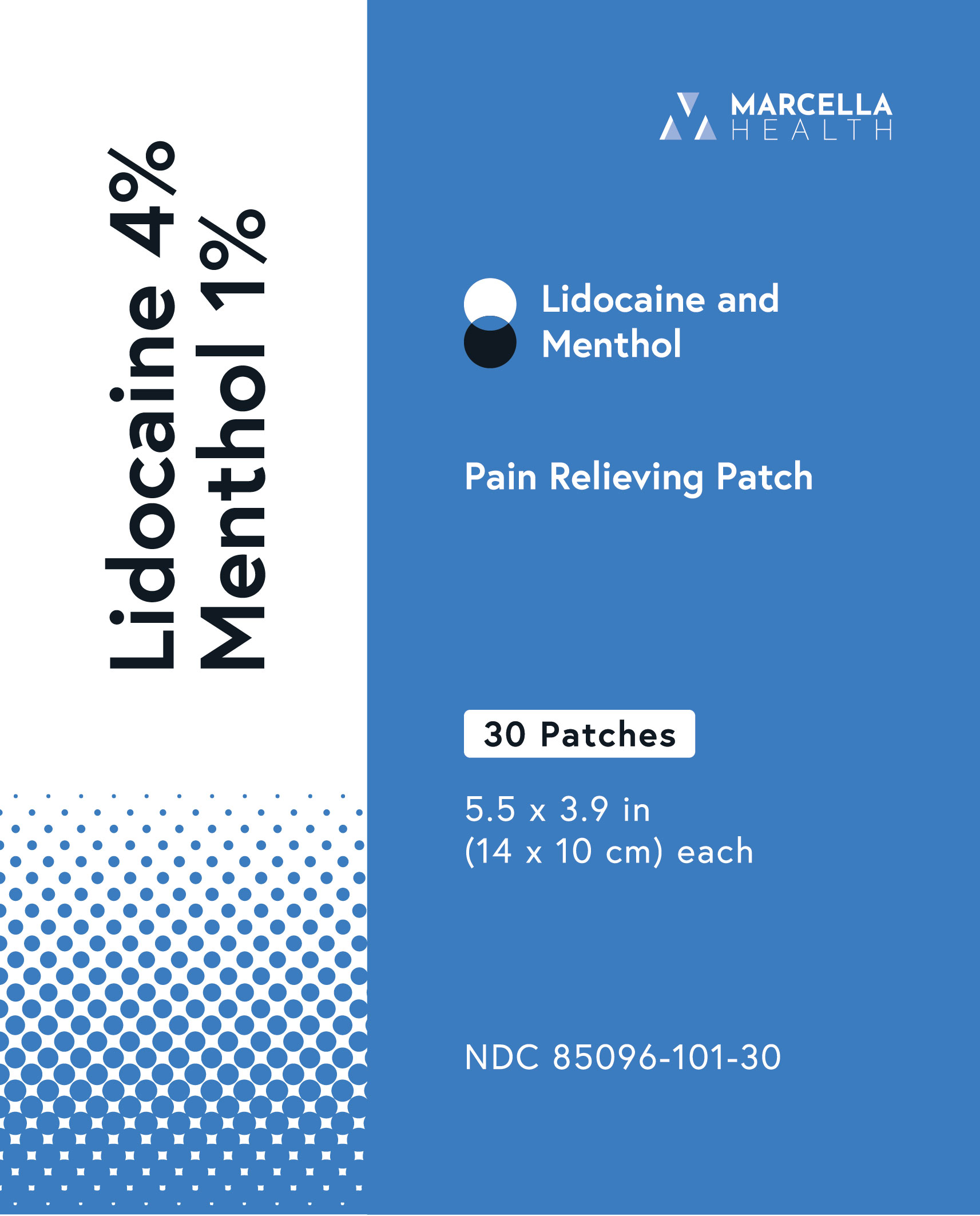 DRUG LABEL: Lidocaine and Menthol
NDC: 85096-101 | Form: PATCH
Manufacturer: Marcella Health
Category: otc | Type: HUMAN OTC DRUG LABEL
Date: 20251103

ACTIVE INGREDIENTS: LIDOCAINE 0.04 g/1 g; MENTHOL 0.01 g/1 g
INACTIVE INGREDIENTS: DIHYDROXYALUMINUM AMINOACETATE; EDETATE DISODIUM; GLYCERIN; HYDROXYACETOPHENONE; KAOLIN; MINERAL OIL; POLYACRYLIC ACID (250000 MW); POLYSORBATE 80; POVIDONE K90; PROPYLENE GLYCOL; SODIUM POLYACRYLATE (2500000 MW); TARTARIC ACID; TITANIUM DIOXIDE; WATER

Lidocaine and Menthol Pain Relieving Patch

Active ingredients (in each patch)

Lidocaine 4%

Purpose

External Anesthetic

Active ingredients (in each patch)

Menthol 1%

Purpose

External Analgesic

Use

Temporarily relieves minor pain

Warnings

For external use only

Do not use

- more than one patch on your body at a time
- on cut, irritated or swollen skin
- on puncture wounds
- for more than one week without consulting a doctor
- if you are allergic to any active or inactive ingredients
- if pouch is damaged or opened

When using this

- use only as directed
- read and follow all directions and warnings on this carton
- do not allow contact with the eyes
- do not use at the same time as other topical analgesics
- do not bandage tightly or apply local heat (such as heating pads) to the area of use
- do not microwave
- dispose of used patch in manner that always keeps product away from children and pets. Used patches still contain the drug product that can produce serious adverse effects if a child or pet chews or ingests this patch.

Stop use and consult a doctor if

- condition worsens
- redness is present
- irritation develops
- symptoms persist for more than 7 days or clear up and occur again within a few days
- you experience signs of skin injury, such as pain, swelling, or blistering where the product was applied

If pregnant or breastfeeding,

ask a health professional before use.

Keep out of reach of children and pets.

If swallowed, get medical help or contact a Poison Control Center 1-800-222-1222 right away.

Directions

Adults and children 12 years of age and over:clean and dry affected area, free of lotions, ointments, and creams. Carefully remove backing from patch starting at a corner. Apply sticky side of patch to affected area. Do not use more than one patch in a 12-hour period. Maximum 2 patches per day. Discard patch after single use.
Children under 12 years of age:consult a physician.

Other information

Store in a clean, dry place outside of direct sunlight. Protect from excessive moisture.

Inactive ingredients

dihydroxyaluminum aminoacetate, edetate disodium, glycerin, hydroxyacetophenone, kaolin, mineral oil, polyacrylic acid, polysorbate 80, povidone K90, propylene glycol, sodium polyacrylate, tartaric acid, titanium dioxide, water

Questions or comments?

Call (307) 410-3813 or email info@marcellahealth.com